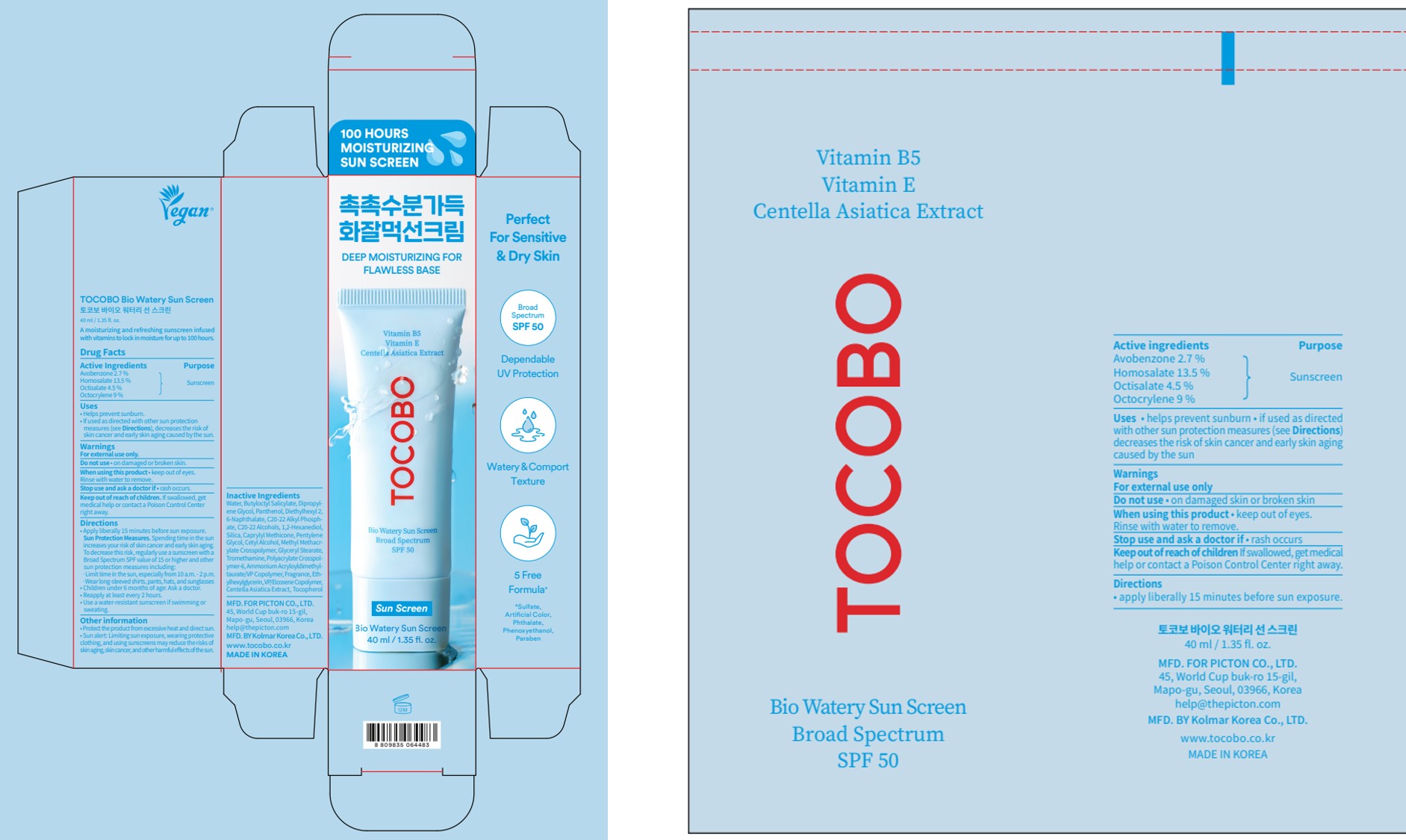 DRUG LABEL: TOCOBO Bio Watery Sun Screen
NDC: 85287-140 | Form: CREAM
Manufacturer: PICTON CO., Ltd.
Category: otc | Type: HUMAN OTC DRUG LABEL
Date: 20251014

ACTIVE INGREDIENTS: OCTISALATE 1.8 g/40 mL; OCTOCRYLENE 3.6 g/40 mL; HOMOSALATE 5.4 g/40 mL; AVOBENZONE 1.08 g/40 mL
INACTIVE INGREDIENTS: CENTELLA ASIATICA TRITERPENOIDS; 1,2-HEXANEDIOL; TROMETHAMINE; ETHYLHEXYLGLYCERIN; TOCOPHEROL; POLYACRYLATE CROSSPOLYMER-6; BUTYLOCTYL SALICYLATE; DIPROPYLENE GLYCOL; PANTHENOL; C20-22 ALCOHOLS; PENTYLENE GLYCOL; AMMONIUM ACRYLOYLDIMETHYLTAURATE/VP COPOLYMER; SILICA; CETYL ALCOHOL; WATER; DIETHYLHEXYL 2,6-NAPHTHALATE; C20-22 ALKYL PHOSPHATE; CAPRYLYL METHICONE; GLYCERYL STEARATE

TOCOBO Bio Watery Sun Screen

Active Ingredients

Avobenzone 2.7 %

Homosalate 13.5 %

Octisalate 4.5 %

Octocrylene 9 %

Purpose

Sunscreen

Uses

• Helps prevent sunburn
• If used as directed with other sun protection measures (see Directions), decreases the risk of skin cancer and early skin aging caused by the sun

Warnings

For external use only

Do not use

• on damaged or broken skin

When using this product

• keep out of eyes. Rinse with water to remove.

Stop use and ask a doctor

• if rash occurs

Keep out of reach of children.

If swallowed, get medical help or contact a Poison Control Center right away.

Directions

• apply liberally 15 minutes before sun exposure. Sun Protection Measures.Spending time in the sun increases your risk of skin cancer and early skin aging. To decrease this risk, regularly use a sunscreen with a Broad Spectrum SPF value of 15 or higher and other sun protection measures including:
·limit time in the sun, especially from 10 a.m. - 2 p.m.
·wear long-sleeved shirts, pants, hats, and sunglasses
• children under 6 months of age: Ask a doctor
• reapply at least every 2 hours
• use a water-resistant sunscreen if swimming or sweating

Other information

• protect the product from excessive heat and direct sun
• Sun alert: Limiting sun exposure, wearing protective clothing, and using sunscreens may reduce the risks of skin aging, skin cancer, and other harmful eﬀects of the sun.

Inactive Ingredients

Water, Butyloctyl Salicylate, Dipropylene Glycol, Panthenol, Diethylhexyl 2, 6-Naphthalate, C20-22 Alkyl Phosphate, C20-22 Alcohols, 1,2-Hexanediol, Silica, Caprylyl Methicone, Pentylene Glycol, Cetyl Alcohol, Methyl Methacrylate Crosspolymer, Glyceryl Stearate, Tromethamine, Polyacrylate Crosspolymer6, Ammonium Acryloyldimethyltaurate/VP Copolymer, Fragrance, Ethylhexylglycerin, VP/Eicosene Copolymer, Centella Asiatica Extract, Tocopherol